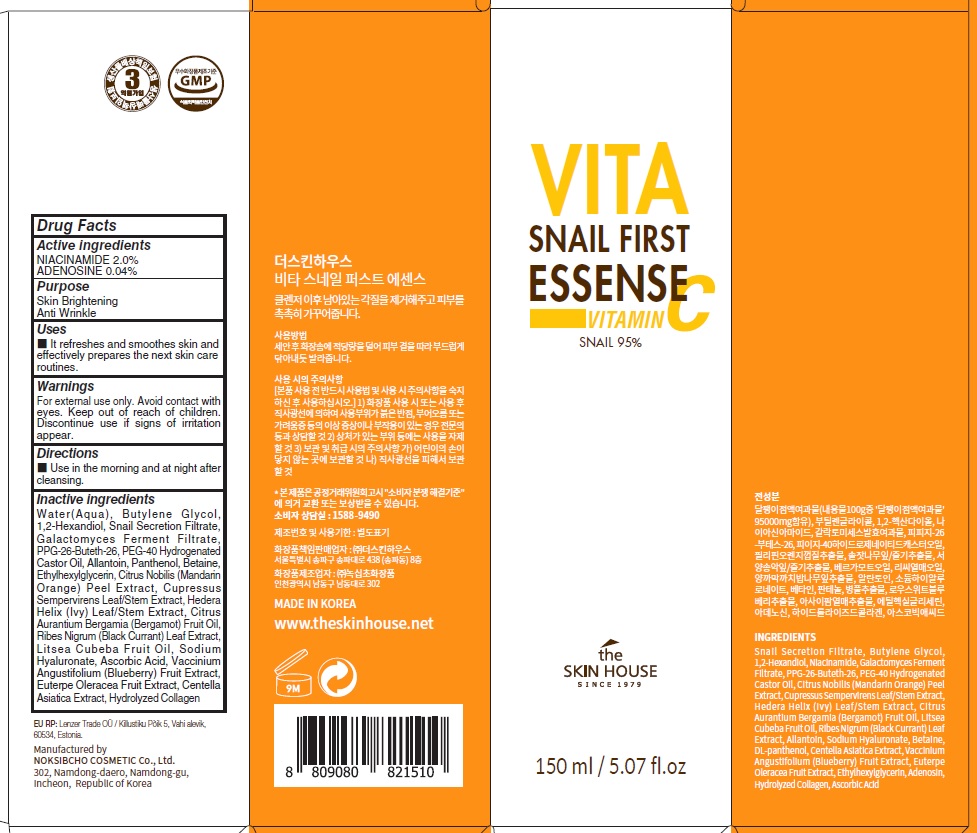 DRUG LABEL: THE SKINHOUSE VITA SNAIL FIRST ESSENSE
NDC: 73590-0082 | Form: LIQUID
Manufacturer: NOKSIBCHO cosmetic Co., Ltd.
Category: otc | Type: HUMAN OTC DRUG LABEL
Date: 20210715

ACTIVE INGREDIENTS: NIACINAMIDE 3.0 g/150 mL; ADENOSINE 0.06 g/150 mL
INACTIVE INGREDIENTS: Water; Butylene Glycol

Drug Facts

ACTIVE INGREDIENT

NIACINAMIDE 2.0%
ADENOSINE 0.04%

INACTIVE INGREDIENTS

Water(Aqua), Butylene Glycol, 1,2-Hexandiol, Snail Secretion Filtrate, Galactomyces Ferment Filtrate, PPG-26-Buteth-26, PEG-40 Hydrogenated Castor Oil, Allantoin, Panthenol, Betaine, Ethylhexylglycerin, Citrus Nobilis (Mandarin Orange) Peel Extract, Cupressus Sempervirens Leaf/Stem Extract, Hedera Helix (Ivy) Leaf/Stem Extract, Citrus Aurantium Bergamia (Bergamot) Fruit Oil, Ribes Nigrum (Black Currant) Leaf Extract, Litsea Cubeba Fruit Oil, Sodium Hyaluronate, Ascorbic Acid, Vaccinium Angustifolium (Blueberry) Fruit Extract, Euterpe Oleracea Fruit Extract, Centella Asiatica Extract, Hydrolyzed Collagen

PURPOSE

Skin Brightening
Anti wrinkle

WARNINGS

For external use only.
Avoid contact with eyes.
Keep out of reach of children.
Discontinue use if signs of irritation appear.

KEEP OUT OF REACH OF CHILDREN

Uses

■ It refreshes and smoothes skin and effectively prepares the next skin care routines.

Directions

■ Use in the morning and at night after cleansing.